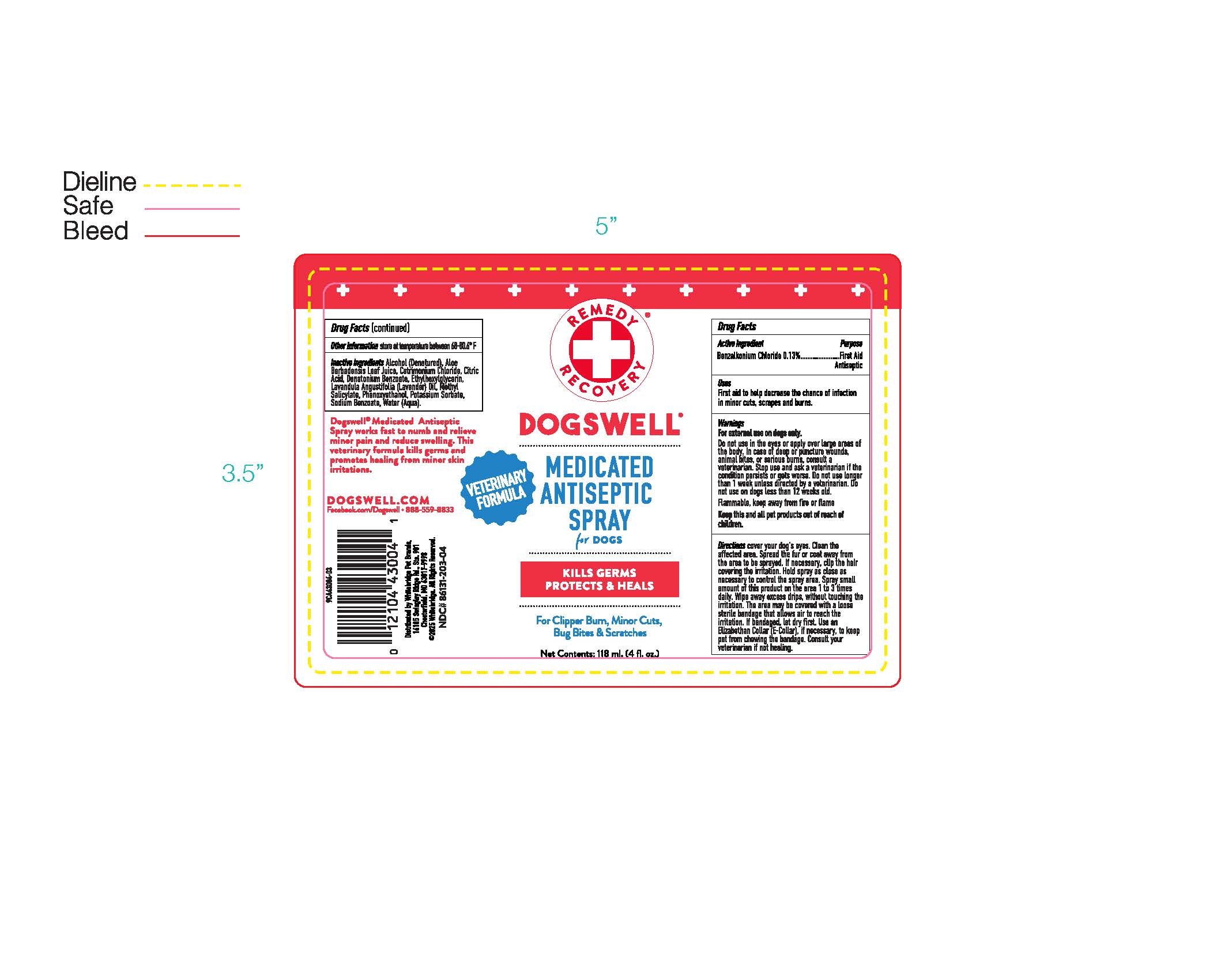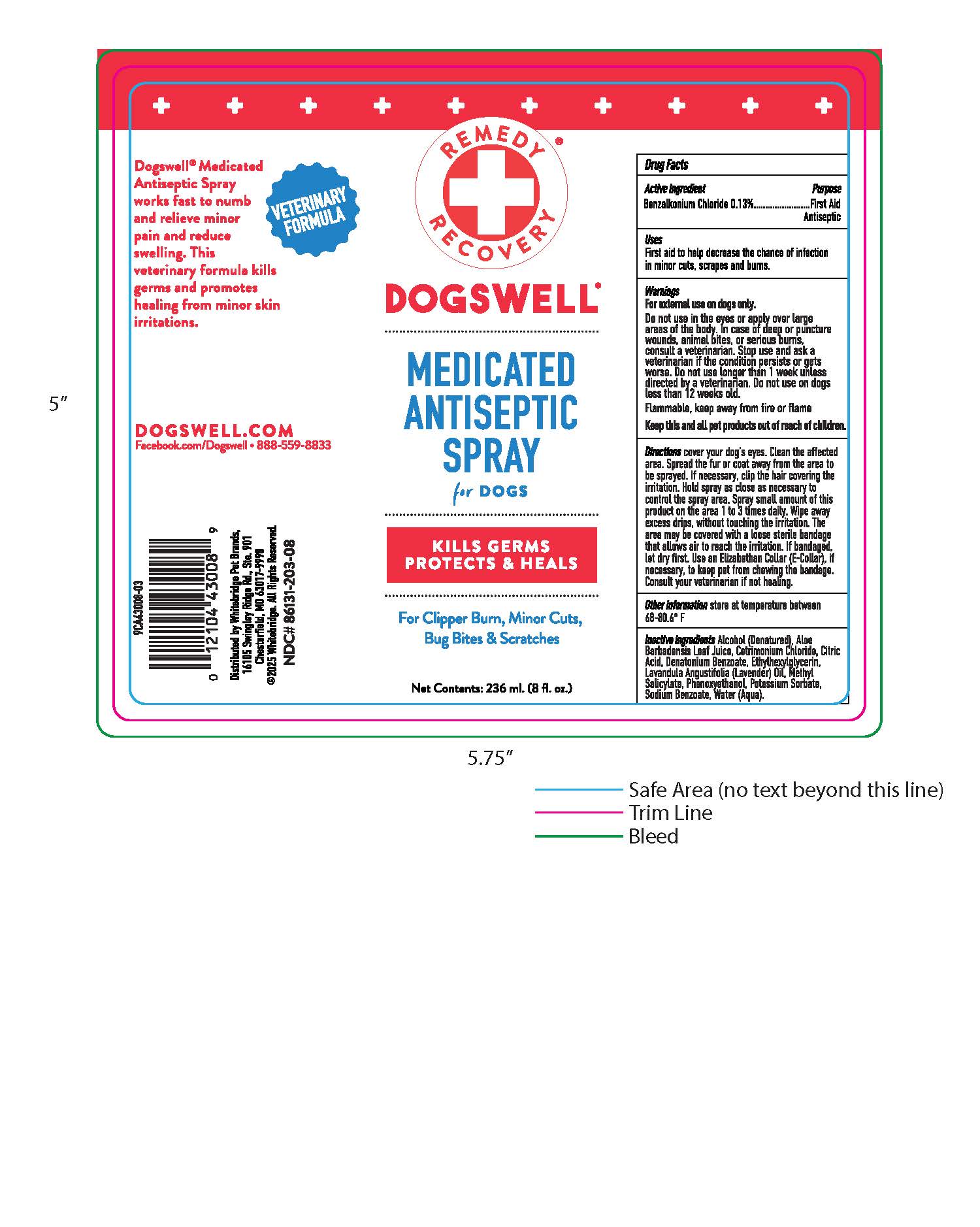 DRUG LABEL: Antiseptic
NDC: 86131-203 | Form: SPRAY
Manufacturer: Whitebridge Pet Brands
Category: animal | Type: OTC ANIMAL DRUG LABEL
Date: 20260123

ACTIVE INGREDIENTS: BENZALKONIUM CHLORIDE 0.13 g/1 g
INACTIVE INGREDIENTS: water; ALCOHOL; DENATONIUM BENZOATE; METHYL SALICYLATE; ALOE VERA LEAF; CETRIMONIUM CHLORIDE; EUCALYPTUS OIL; PHENOXYETHANOL; ETHYLHEXYLGLYCERIN

Medicated Antiseptic Spray

DRUG FACTS

Active Ingredients Purpose

Benzalkonioum Chloride 0.13% ....... First Aid Antiseptic

PURPOSE

First Aid Antiseptic

Uses

First aid to help decrease the chance of infection in minor cuts, scrapes and burns.

Warnings

For external use on dogs only. Do not use in the eyes or apply over large areas of the body. In case of deep or puncture wounds, animal bites, or serious burns, consult a veterinarian. Stop use and ask a veterinarian if the condition persists or gets worse. Do not use longer than 1 week unless directed by a veterinarian. Do not use on dogs less than 12 weeks old.

Keep this and all pet prosucts out of reach of childern.

Directions

cover your dog's eyes. Clean the affected area. Spread the fur or coat away from the area to be sprayed. If necessary, clip the hair covering the irritation. Hold spray as close as necessary to control the spray area. Spray small amounts of this product on the area 1 to 3 times daily. Wipe away excess drips, without touching the irritation. The area may be covered with loose sterile bandage that allows air to reach the irritation. If bandaged let dry first. Use an Elizabethan Collar (E-Collar), if necessary, to keep pet from chewing the bandage. Consult your veterinarian if not healing.

Other information

store at temperature between 68-80.6 F

Inactive ingredients

Alcohol (Denatured), Aloe Barbadensis Leaf Juice, Cetrimonium Chloride, Citric acid, Denatonium Benzoate, Ethylhexylglcerin, Lavandula Angustifolia (Lavender) Oil, Methyl Salicylate, Phenoxyethanol, Potassium Sorbate, Sodium Benzoate, Water (Aqua).

Dogswell Medicated Antiseptic Spray works fast to numb and relieve minor pain and reduce swelling. This veterinary formula kills germs and promoites healing from minor skin irritations.

DOGSWELL.COM

Facebook.com/Dogswell 888-559-8833

Distributed by Whitebridge Pet Brands,

St. Louis, MO 63141

2020 Whitebridge. All Rights Reserved.

NDC# 86131-203-08

PACKAGE LABEL

Remedy Recovery

Dogswell

Medicated Antiseptic Spray

for DOGS

KILLS GERMS PROTECTS & HEALS

For Clipper Burn, Minor Cuts, Bug Bites & Scratches

Net Contents: 236 ml. (8 fl. oz.)